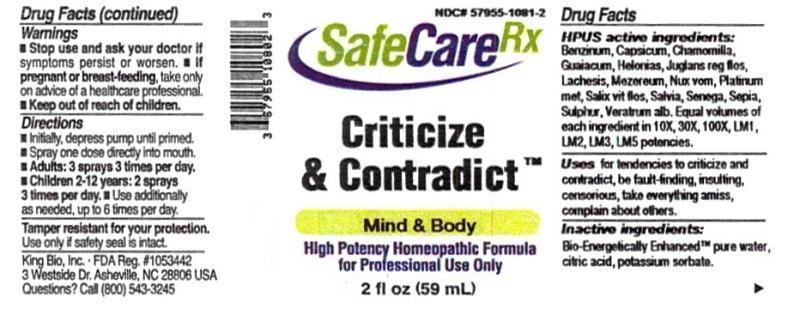 DRUG LABEL: Criticize and Contradict
NDC: 57955-1081 | Form: LIQUID
Manufacturer: King Bio Inc.
Category: homeopathic | Type: HUMAN OTC DRUG LABEL
Date: 20160401

ACTIVE INGREDIENTS: BENZENE 10 [hp_X]/59 mL; CAPSICUM 10 [hp_X]/59 mL; MATRICARIA RECUTITA 10 [hp_X]/59 mL; GUAIACUM OFFICINALE RESIN 10 [hp_X]/59 mL; CHAMAELIRIUM LUTEUM ROOT 10 [hp_X]/59 mL; JUGLANS REGIA FLOWERING TOP 10 [hp_X]/59 mL; LACHESIS MUTA VENOM 10 [hp_X]/59 mL; DAPHNE MEZEREUM BARK 10 [hp_X]/59 mL; STRYCHNOS NUX-VOMICA SEED 10 [hp_X]/59 mL; PLATINUM 10 [hp_X]/59 mL; SALIX ALBA FLOWERING TOP 10 [hp_X]/59 mL; SAGE 10 [hp_X]/59 mL; POLYGALA SENEGA ROOT 10 [hp_X]/59 mL; SEPIA OFFICINALIS JUICE 10 [hp_X]/59 mL; SULFUR 10 [hp_X]/59 mL; VERATRUM ALBUM ROOT 10 [hp_X]/59 mL
INACTIVE INGREDIENTS: WATER; ANHYDROUS CITRIC ACID; POTASSIUM SORBATE

Criticize and Contradict™

ACTIVE INGREDIENT

Drug Facts__________________________________________________________________________________________________________

HPUS active ingredients: Benzinum, Capsicum annuum, Chamomilla, Guaiacum, Helonias dioica, Juglans regia, flos, Lachesis mutus, Mezereum, Nux vomica, Platinum metallicum, Salix vitellina, flos, Salvia officinalis, Senega officinalis, Sepia, Sulphur, Veratrum album. Equal volumes of each ingredient in 10X, 30X, 100X, LM1, LM2, LM3, LM5 potencies.

INDICATIONS AND USAGE

Uses for tendencies to criticize and contradict, be fault-finding, insulting, censorious, take everthing amiss, complain about others.

Inactive Ingredients:

Bio-Energetically Enhanced™ pure water, citric acid and potassium sorbate.

Warnings

- Stop use and ask your doctor if symptoms persist or worsen.
- If pregnant or breast-feeding, take only on advice of a healthcare professional.

- Keep out of reach of children.

Directions

- Initially, depress pump until primed.
- Spray one dose directly into mouth.
- Adults: 3 sprays 3 times per day.
- Children 2-12 years: 2 sprays 3 times per day.
- Use additionally as needed, up to 6 times per day.

OTHER SAFETY INFORMATION

Tamper resistant for your protection. Use only if safety seal is intact.

PURPOSE

Uses for tendencies to criticize and contradict:

- be fault-finding
- insulting
- censorious
- take everthing amiss
- complain about others